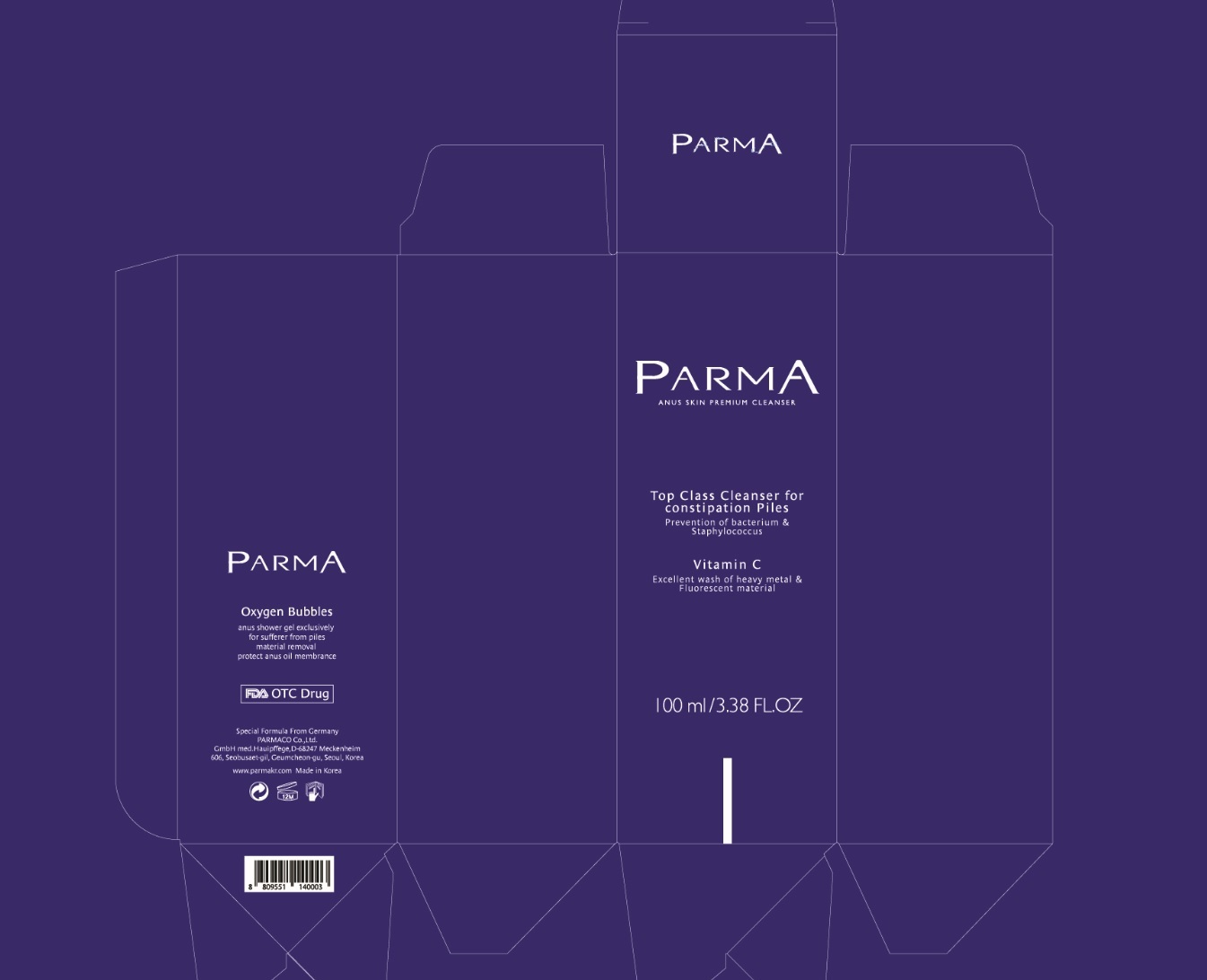 DRUG LABEL: Parma Anus Skin Premium Cleanser
NDC: 71614-002 | Form: GEL
Manufacturer: PARMA KOREA
Category: otc | Type: HUMAN OTC DRUG LABEL
Date: 20251002

ACTIVE INGREDIENTS: ALLANTOIN 3 mg/1 mL
INACTIVE INGREDIENTS: SAPINDUS MUKOROSSI FRUIT; ASIAN GINSENG; POLYSORBATE 85; 1,2-HEXANEDIOL; MEDIUM-CHAIN TRIGLYCERIDES; WATER; HYDROXYETHYL CELLULOSE (100 MPA.S AT 2%); MANDELIC ACID; EDETATE DISODIUM ANHYDROUS; OLEIC ACID; LAURYL GLUCOSIDE; BUTYLENE GLYCOL; DIGLYCERIN; SODIUM COCOATE; COCO MONOISOPROPANOLAMIDE; NEPIDERMIN; ACETYL HEXAPEPTIDE-8; SODIUM COCOAMPHOACETATE; RICE BRAN; ARTEMISIA VULGARIS ROOT; MUNG BEAN; CENTELLA ASIATICA; PURSLANE; RHEUM PALMATUM ROOT; BAMBUSA VULGARIS TOP; EUCALYPTUS GLOBULUS LEAF; HAMAMELIS VIRGINIANA TOP; MATRICARIA CHAMOMILLA FLOWERING TOP; PROPOLIS WAX

71614-002_Parma Anus Skin Premium Cleanser

ACTIVE INGREDIENT

Allantoin 0.3%

PURPOSE

Skin Protectant

INDICATIONS AND USAGE

Anus Cleansing

DOSAGE AND ADMINISTRATION

Wet anal area thoroughly.

Apply an appropriate amount of the product to anal area. Massage anus and maintain 30 seconds. Rinse with water for 60 seconds.

WARNINGS

For external use only.

Do not use on damaged or broken skin.

Rinse with water to remove.

Stop use and ask a doctor if rash or irritation occurs.

Keep out of reach of children

INACTIVE INGREDIENT

Water
Hydroxyethylcellulose
Black Strap Powder
Mandelic Acid
Disodium EDTA
Oleic Acid
Lauryl Glucoside
Butylene Glycol
Diglycerin
Sodium Cocoate
Cocamide MIPA
sh-Oligopeptide-1
Acetyl Hexapeptide-8
Shea Butteramidopropyl Betaine
Sodium Cocoamphoacetate
Oryza Sativa (Rice) Bran Extract
Artemisia Vulgaris Extract
Phaseolus Radiatus Seed Extract
Centella Asiatica Extract
Portulaca Oleracea Extract
Crataegus Oxyacantha Extract
Rheum Palmatum Root Extract
Bambusa Vulgaris Extract
Eucalyptus Globulus Leaf Extract
Hamamelis Virginiana (Witch Hazel) Extract
Chamomilla Recutita (Matricaria) Flower/Leaf Extract
Propolis Extract
Sapindus Mukorossi Fruit Extract
Panax Ginseng Root Extract
Polysorbate 85
1,2-Hexanediol
Caprylic/Capric Triglyceride
Fragrance